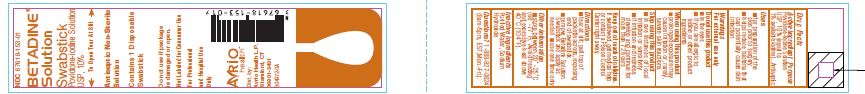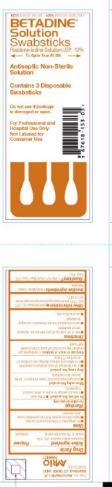 DRUG LABEL: Betadine
NDC: 67618-153 | Form: SOLUTION
Manufacturer: Atlantis Consumer Healthcare, Inc.
Category: otc | Type: HUMAN OTC DRUG LABEL
Date: 20251111

ACTIVE INGREDIENTS: POVIDONE-IODINE 10 mg/1 mL
INACTIVE INGREDIENTS: SODIUM HYDROXIDE; WATER

BETADINE® Solution Swabstick
Povidone-iodineSolution USP, 10%
Drug Facts

Active ingredient Purpose

Povidone-iodine Solution USP, 10% (equal to1% available iodine)

Purpose

Antiseptic

Uses

- for preparation of the skin prior to surgery
- helps reduce bacteria that can potentially cause skin infection

Warnings

For external use only

Do not use this product

- in the eyes
- if you are allergic to iodine or other product ingredients

When using this product

- prolonged exposure may cause irritation or, rarely, severeskin reactions

Stop using this product

- in rare instances of local irritation or sensitivity
- if irritation and redness develop and continue for morethan 72 hours

Keep out of reach ofchildren.

Ifswallowed, get medical help or contact a Poison Control Center rightaway

Directions

- tear at slit; pull top of packette across, exposing endof swabstick
- remove Betadine Solution Swabstick and apply as needed
- use one time only

Other information

store between 20˚-25˚C (68˚-77˚F).Avoid freezing and excessive heat above 40˚C (104˚F).

Inactive ingredients

purified water, sodium hydroxide

Dist. by:
Avrio Health L.P.
Stamford, CT 06901-3431

PACKAGE LABEL

BetadineSwabsticks — 1 Swab
NDC: 67618-153-01

BetadineSwabsticks — 3 Swabs
67618-153-03